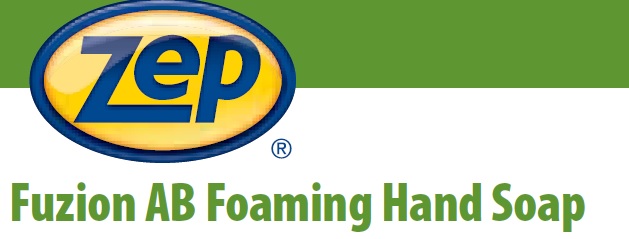 DRUG LABEL: Fuzion AB Foam
NDC: 66949-111 | Form: LIQUID
Manufacturer: Zep Inc.
Category: otc | Type: HUMAN OTC DRUG LABEL
Date: 20251226

ACTIVE INGREDIENTS: BENZALKONIUM CHLORIDE 0.13 g/100 mL
INACTIVE INGREDIENTS: METHYLISOTHIAZOLINONE; FD&C RED NO. 4; ANHYDROUS CITRIC ACID; GLUTARAL; FD&C YELLOW NO. 5; CETRIMONIUM CHLORIDE; DI-PPG-2 MYRETH-10 ADIPATE; METHYLCHLOROISOTHIAZOLINONE; WATER; LAUROYL/MYRISTOYL AMIDOPROPYL AMINE OXIDE; GLYCERIN; TETRASODIUM IMINODISUCCINATE

66949-111 / 3388 Fuzion AB Foam

Active ingredient

Benzalkonium Chloride 0.13%

Purpose

Antibacterial Hand Wash

Uses

For washing to decrease bacteria on hands.

Warnings

For external use only.

Do not use in the eyes; if in eyes, rinse promptly and thoroughly with water.

When using this product

- Do not swallow.
- If swallowed, do not induce vomiting and if individual is conscious, give large quantities of water to drink and consult a physician immediately.

Stop use and ask a doctor if skin irritation or redness persists for more than 72 hours.

Keep out of reach of children and pets. Children must be supervised in use of this product.

Directions

- Wet hands with water.
- Press pump to dispense product into hands.
- Massage soap into hands and wrists, emphasizing back of hands, knuckles and cuticles.
- Rinse hands thoroughly and dry.
- Store at 20 to 25°C (68 to 77°F).
- Dispose in accordance with all applicable federal, state and local regulations.

Inactive Ingredients

Water, Cetrimonium Chloride, Lauryl/Myristyl Amidopropyl Amine Oxide, Glycerin, Di-PPG-2 Myreth-10 Adipate, Tetrasodium Iminodisuccinate, Methylchloroisothiazolinone, Methylisothiazolinone, Fragrance, Glutaral, Citric Acid, Red 4, Yellow 5

Questions or comments?

Call 1-800-I-BUY-ZEP (1-800-428-9937)